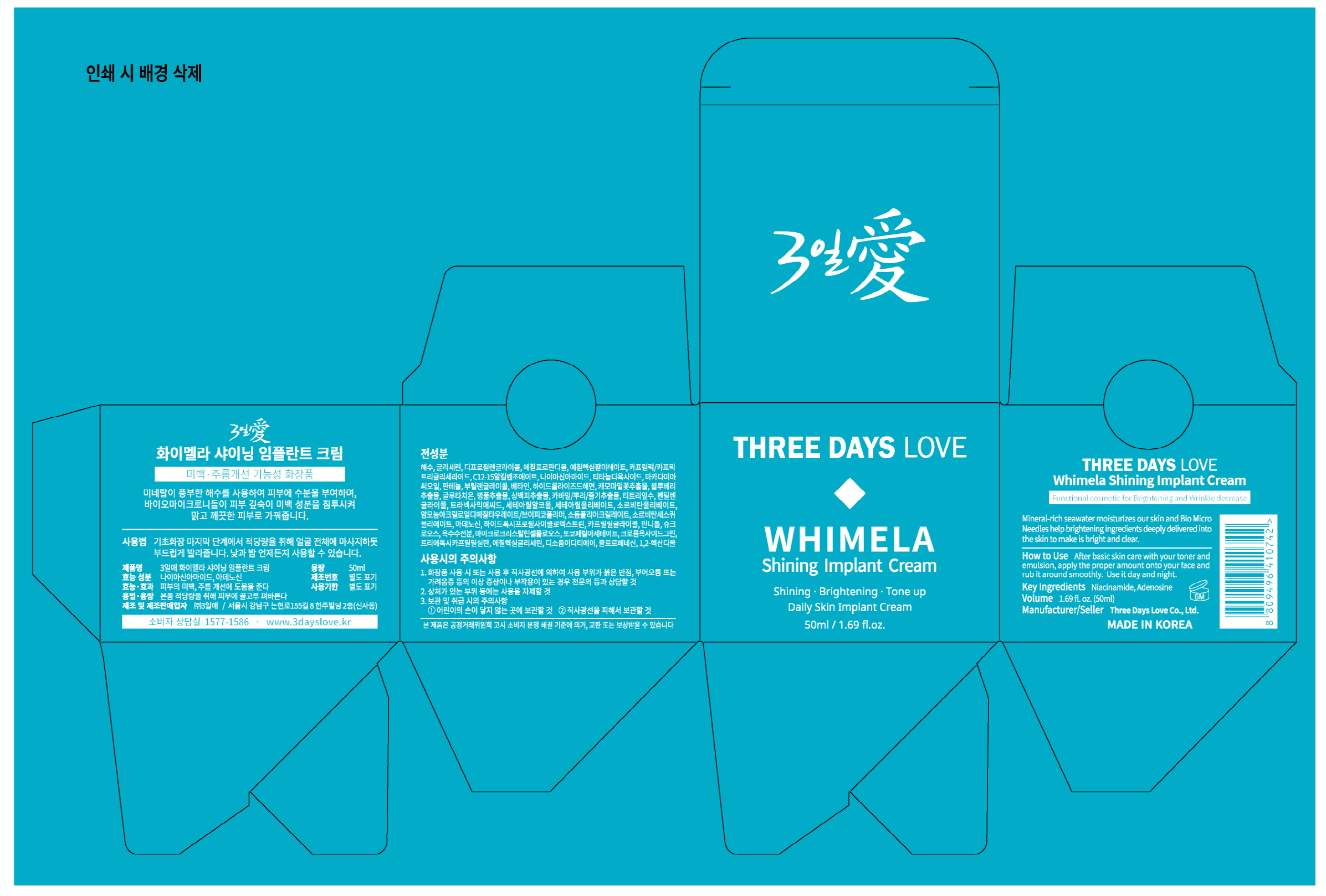 DRUG LABEL: Whimela Shining Implant
NDC: 72368-0002 | Form: CREAM
Manufacturer: Threedayslove Co., Ltd.
Category: otc | Type: HUMAN OTC DRUG LABEL
Date: 20200103

ACTIVE INGREDIENTS: GLYCERIN 8 g/100 g
INACTIVE INGREDIENTS: NIACINAMIDE; WATER; BUTYLENE GLYCOL; ADENOSINE

Drug Facts

ACTIVE INGREDIENT

Glycerin

INACTIVE INGREDIENT

Water, Niacinamide, Adenosine, Butylene Glycol, etc.

PURPOSE

Skin Protectant

keep out of reach of the children

INDICATIONS AND USAGE

How To Use: Gently shake and spray proper amount to desired area. Also use it frequently onto the dried skin and irritated skin.

WARNINGS

Precautions

1. If the cosmetic causes red rash, swollenness or itching by exposure to sunlight during the use, you are advised to stop using it immediately and you may consult a pharmacist or a doctor

2. It is not advised to use the cosmetic on the skin where you have scars

3. Precautions for storage

ⓐ Keep it out of infants or children’s reach

ⓑ Keep it out of the place where exposure to direct sunlight exists

DOSAGE AND ADMINISTRATION

for external use only